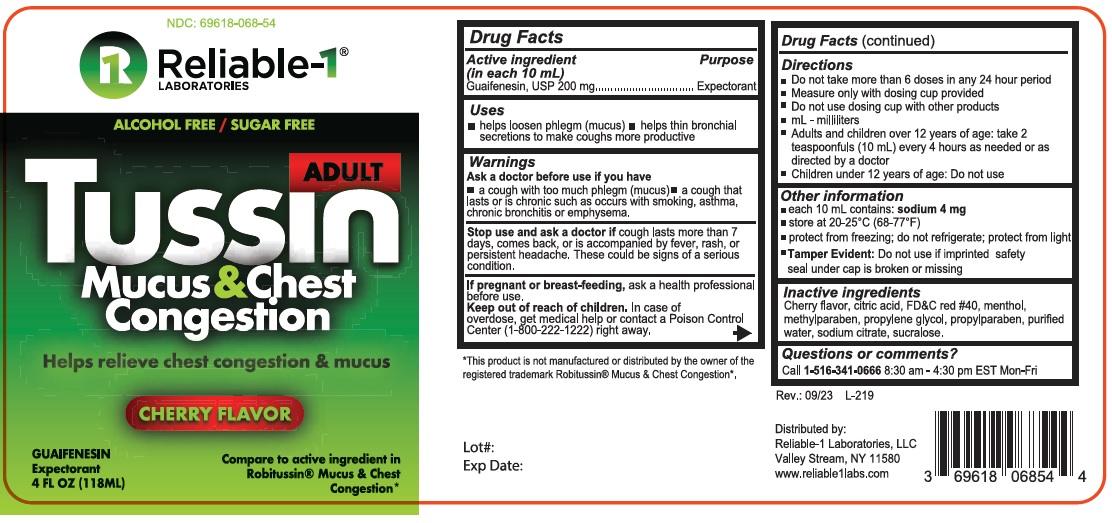 DRUG LABEL: Reliable-1 Tussin
NDC: 69618-068 | Form: LIQUID
Manufacturer: RELIABLE 1 LABORATORIES LLC
Category: otc | Type: HUMAN OTC DRUG LABEL
Date: 20260102

ACTIVE INGREDIENTS: GUAIFENESIN 100 mg/5 mL
INACTIVE INGREDIENTS: ANHYDROUS CITRIC ACID; FD&C RED NO. 40; MENTHOL; METHYLPARABEN; PROPYLENE GLYCOL; PROPYLPARABEN; WATER; SODIUM CITRATE; SUCRALOSE

Reliable-Tussin 068

ACTIVE INGREDIENT

In each 10 mL

Guaifenesin - 200 mg

Purpose

Expectorant

Uses

- helps loosen phlegm (mucus)
- helps thin bronchial secretions to make coughs more productive

Warnings

Ask a doctor before use if you have

- a cough with too much phlegm (mucus)
- a cough that lasts or is chronic such as occurs with smoking, asthma, chronic bronchitis or emphysema

Stop use and ask a doctor if cough lasts more than 7 days, comes back, or is accompnaied by fever, rash, or persistent headache. These could be signs of a serious condition.

PREGNANCY OR BREAST FEEDING

If pregnant or breast-feeding,ask a health professional before use.

Keep out of reach of children. In case of overdose, get medical help or contact a Poison Control Center right away

Directions

- Do not take more tha 6 doses in any 24 hour period
- Measure only with dosing cup provided
- mL- mililiters
- Adults and children over 12 years of age: take 2 teaspoonfuls (10 mL) every 4 hours as needed or as directed by a doctor
- Children under 12 years of age: Do not use

INACTIVE INGREDIENT

Inactive ingredients: cherry flavor, citric acid, FD&C red #40, menthol, methylparaben, propylene glycol, propylparaben, purified water, sodium citrate, sucralose

Questions or comments? 1-516-341-0666 8:30 am - 4:30 pm EST Mon-Fri